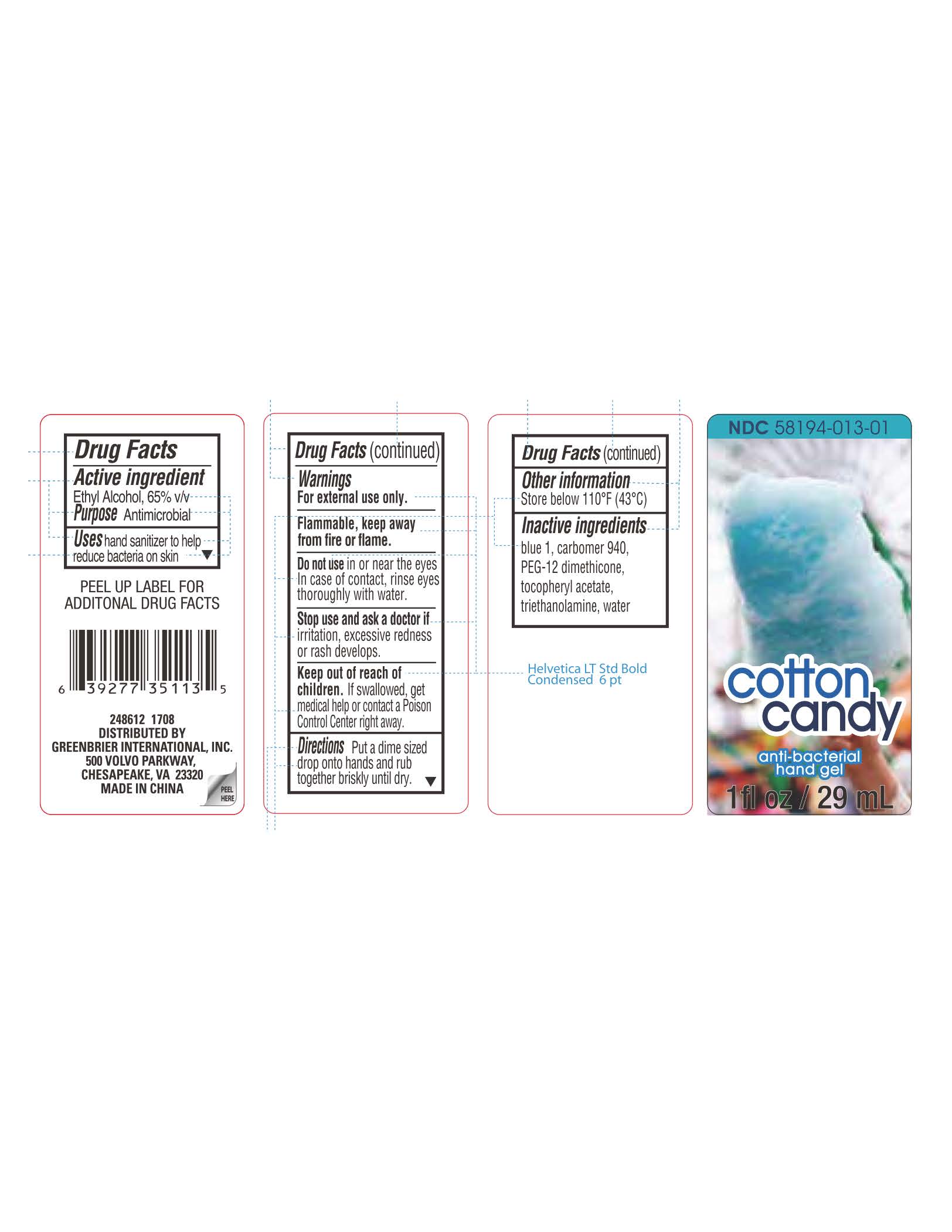 DRUG LABEL: Cotton Candy
                
NDC: 71537-003 | Form: LIQUID
Manufacturer: Huijing (Shanghai) Bio-tech Co., Ltd
Category: otc | Type: HUMAN OTC DRUG LABEL
Date: 20170623

ACTIVE INGREDIENTS: ALCOHOL 65 mL/100 mL
INACTIVE INGREDIENTS: CARBOMER HOMOPOLYMER TYPE C (ALLYL PENTAERYTHRITOL CROSSLINKED); PEG-12 DIMETHICONE (300 CST); PROPYLENE GLYCOL; .ALPHA.-TOCOPHEROL ACETATE; TROLAMINE; FD&C BLUE NO. 1; WATER

Drug Facts

Inactive Ingredients

blue 1, carbomer 940, PEG-12

dimethicone, tocopheryl

acetate, triethanomaline,

water

Active Ingredient

Ethyl Alcohol, 65 % v/v

Purpose Antimicrobial

Uses

hand sanitizer to help

reduce bacteria on skin

Do not use in or near the eyes.

In case of contact, rinse eyes

thoroughly with water.

Stop use and ask a doctor if

irritation, excessive redness

or rash develops.

Keep out of reach of children.

If swallowed, get medical help or contact a Poison

Control Center right away.

Directions

Put a dime sized drop onto hands

and rub together briskly until dry.

Other information

Store below 110 F (43 C)

Warnings

For external use only

Flammable, keep away from fire or flame.